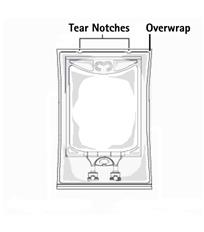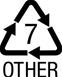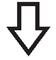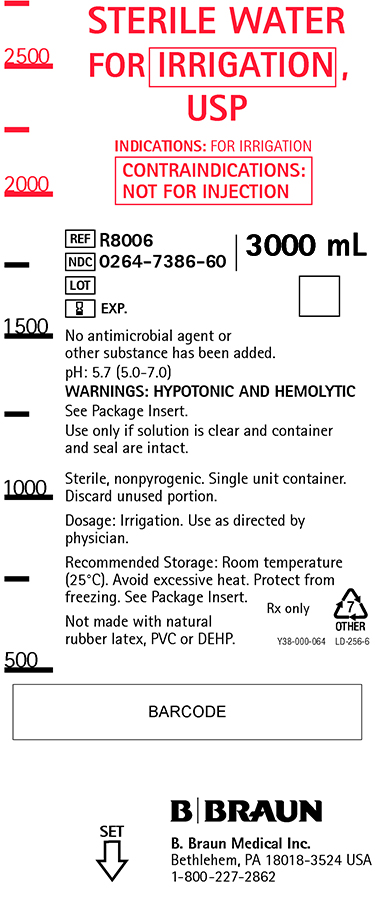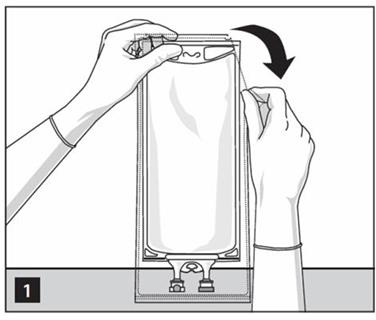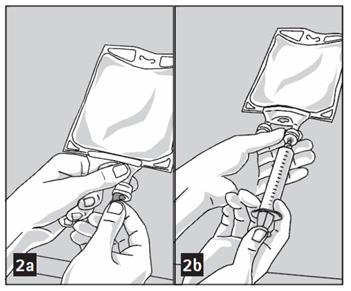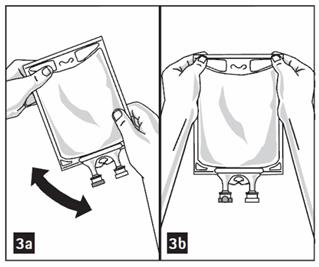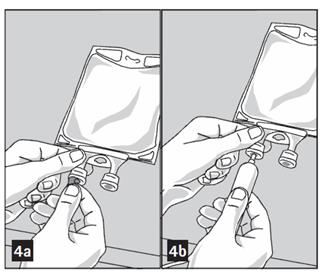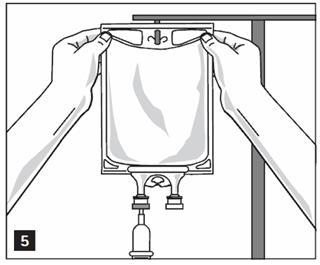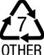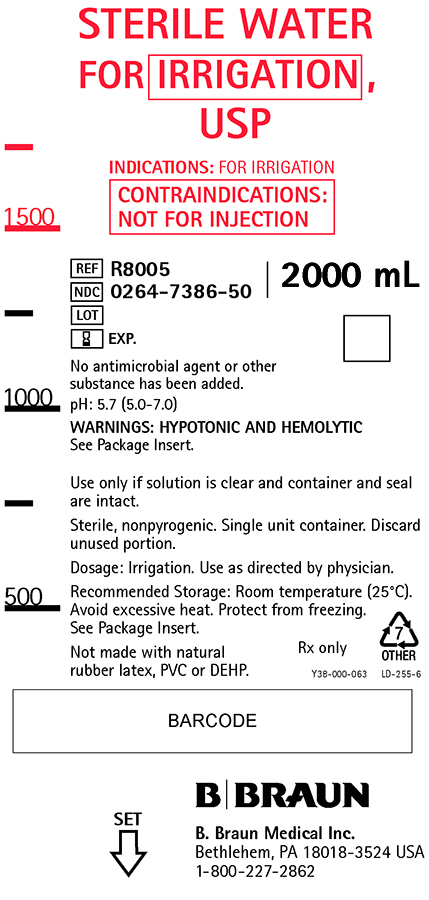 DRUG LABEL: Sterile Water
NDC: 0264-7386 | Form: IRRIGANT
Manufacturer: B. Braun Medical Inc.
Category: prescription | Type: HUMAN PRESCRIPTION DRUG LABEL
Date: 20210809

ACTIVE INGREDIENTS: WATER 100 mL/100 mL

Sterile Water for Irrigation USP

DESCRIPTION

Sterile Water for Irrigation USP is a sterile, hypotonic, nonpyrogenic irrigating fluid or pharmaceutic aid (solvent) entirely composed of Sterile Water for Injection USP. It is prepared by distillation and contains no antimicrobial or bacteriostatic agents or added buffers.
The pH is 5.7 (5.0-7.0)

The plastic container is made from a multilayered film specifically developed for parenteral drugs. It contains no plasticizers and exhibits virtually no leachables. The solution contact layer is a rubberized copolymer of ethylene and propylene. The container is nontoxic and biologically inert. The container-solution unit is a closed system and is not dependent upon entry of external air during administration. The container is overwrapped to provide protection from the physical environment and to provide an additional moisture barrier when necessary.

Not made with natural rubber latex, PVC or DEHP.

CLINICAL PHARMACOLOGY

Sterile Water for Irrigation USP is utilized for a variety of clinical indications. Because of its low refractive index (1.3325), water provides excellent visibility during endoscopic urological procedures. It is also utilized as a pharmaceutic aid, as well as in the preparation of enteral nutrient products.

Water is hypotonic and will cause hemolysis and will be readily absorbed by the tissues during surgical procedures; therefore, its use under such conditions is not recommended.

INDICATIONS AND USAGE

Sterile Water for Irrigation USP is indicated for use as an irrigating fluid or pharmaceutic aid. Sterile Water may also be used as an adjunct in the preparation of non-intravenously administered nutrient mixtures (see DOSAGE AND ADMINISTRATION).

CONTRAINDICATIONS

Not for injection.

WARNINGS

Sterile Water for Irrigation USP is hypotonic and will cause hemolysis, and is not recommended for use during surgical procedures.

After opening container, its contents should be used promptly to minimize the possibility of bacterial growth or pyrogen formation.

Discard unused portion of irrigating solution since it contains no preservative.

PRECAUTIONS

Use only if solution is clear and container and seal are intact.

ADVERSE REACTIONS

None known.

OVERDOSAGE

None known.

DOSAGE AND ADMINISTRATION

Irrigation

Use as directed by physician.

This drug product should be inspected visually for particulate matter and discoloration prior to administration, whenever solution and container permit.

Nutrient Mixtures

Sterile Water for Irrigation USP may be used to prepare non-intravenously administered nutrient mixtures. It contains no electrolytes or other added substances. Refer to preparation instructions of particular mixture to be used. The plastic container may be used for administration of non-intravenous nutrient mixture to the patient as appropriate.

HOW SUPPLIED

Sterile Water for Irrigation USP is supplied sterile and nonpyrogenic in single-dose 2000 and 3000 mL flexible irrigation containers packaged 4 per case.

NDC | REF | SIZE
0264-7386-50 | R8005 | 2000 mL
0264-7386-60 | R8006 | 3000 mL

Exposure of pharmaceutical products to heat should be minimized. Avoid excessive heat. Protect from freezing. It is recommended that the product be stored at room temperature (25°C); however, brief exposure up to 40°C does not adversely affect the product.

Directions for Use of Plastic Container

Not for injection.

Not for use with pressurized irrigation systems.

Aseptic technique is required.

- Inspect irrigation bag: overwrap and primary bag.
- Do not use if overwrap has been damaged.
- Do not use unless solution is clear and closure is intact.

1. To open: Tear overwrap starting from the tear notches. (Figure 1)
2. Prepare medication port by removal of aluminum foil. (Figure 2a)
  - Puncture resealable medication port by using 19 – 22 gauge needle and inject additive(s). (Figure 2b)
  - Mix solution and medication thoroughly. (Figure 3a)
  - Medication port must be swabbed with disinfection agent before re-puncturing.
  - Check admixture visually for particulate matter. (Figure 3b)
3. Remove aluminum foil from outlet/set port at the bottom of container (Figure 4a) and attach administration set (Figure 4b): use non-vented infusion set or close air vent on a vented set. Refer to directions for use accompanying the administration set.
4. Hang bag on IV Pole. (Figure 5)

Rx only

B. Braun Medical Inc.
Bethlehem, PA 18018-3524 USA
1-800-227-2862

LD-401-5 Y36-002-984

Revised: August 2018

PRINCIPAL DISPLAY PANEL

STERILE WATER
FOR IRRIGATION,
USP

INDICATIONS: FOR IRRIGATION

CONTRAINDICATIONS:
NOT FOR INJECTION

REF R8005
NDC 0264-7386-50
LOT
EXP.

2000 mL

No antimicrobial agent or other
substance has been added.

pH: 5.7 (5.0-7.0)

WARNINGS: HYPOTONIC AND HEMOLYTIC

See Package Insert.

Use only if solution is clear and container and seal
are intact.

Sterile, nonpyrogenic. Single unit container. Discard
unused portion.

Dosage: Irrigation. Use as directed by physician.

Recommended Storage: Room temperature (25°C).
Avoid excessive heat. Protect from freezing.
See Package Insert.

Not made with natural
rubber latex, PVC or DEHP.

Rx only

Y38-000-063 LD-255-6

B. Braun Medical Inc.
Bethlehem, PA 18018-3524 USA
1-800-227-2862

SET

Sterile Water Irrigation 2L Container Label

PRINCIPAL DISPLAY PANEL

STERILE WATER
FOR IRRIGATION,
USP

INDICATIONS: FOR IRRIGATION

CONTRAINDICATIONS:
NOT FOR INJECTION

REF R8006
NDC 0264-7386-60
LOT
EXP.

3000 mL

No antimicrobial agent or
other substance has been added.

pH: 5.7 (5.0-7.0)

WARNINGS: HYPOTONIC AND HEMOLYTIC

See Package Insert.

Use only if solution is clear and container
and seal are intact.

Sterile, nonpyrogenic. Single unit container.
Discard unused portion.

Dosage: Irrigation. Use as directed by
physician.

Recommended Storage: Room temperature
(25°C). Avoid excessive heat. Protect from
freezing. See Package Insert.

Not made with natural
rubber latex, PVC or DEHP.

Rx only

Y38-000-064 LD-256-6

B. Braun Medical Inc.
Bethlehem, PA 18018-3524 USA
1-800-227-2862

SET

Sterile Water Irrigation 3L Container Label